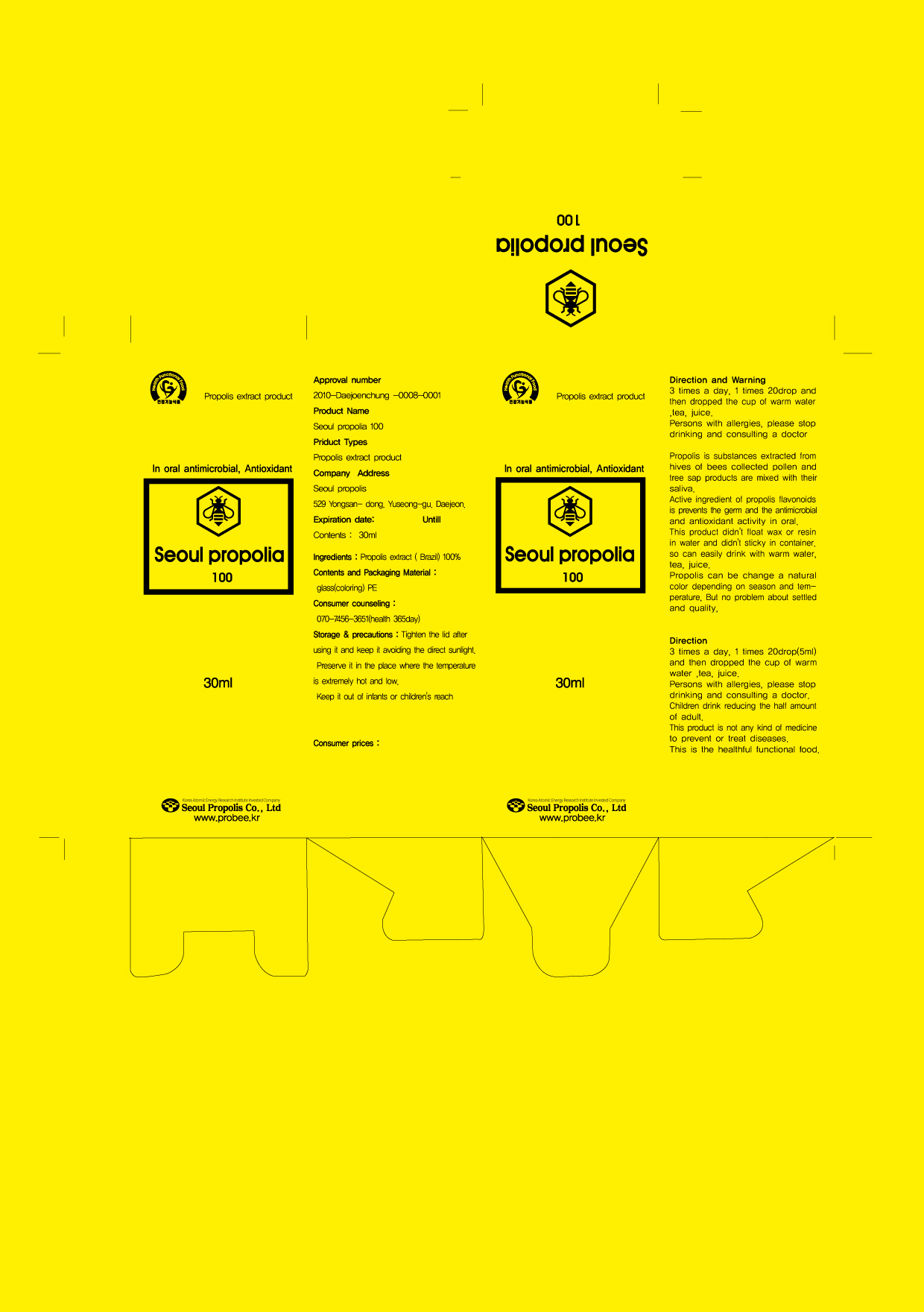 DRUG LABEL: Seoul Propolia
NDC: 76254-5001 | Form: LIQUID
Manufacturer: Seoul Propolis
Category: otc | Type: HUMAN OTC DRUG LABEL
Date: 20110816

ACTIVE INGREDIENTS: PROPOLIS WAX 0.99 mL/1 mL
INACTIVE INGREDIENTS: WATER

Drug Facts

active ingredient: propolis

inactive ingredient: purified water

PURPOSE

anti oxidant for the health
energizing for the life
health maintenance and improvement
to reduce the excessive stress

keep out of reach of the children

INDICATIONS AND USAGE

1 time 20 drops and then dropped the cup and mix with warm water, tea, juice

WARNINGS

keep in a cool place
avode direct sunlight

DOSAGE AND ADMINISTRATION

3 times a day